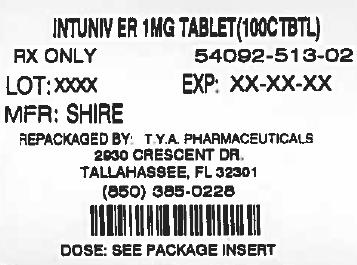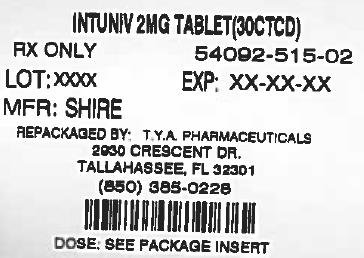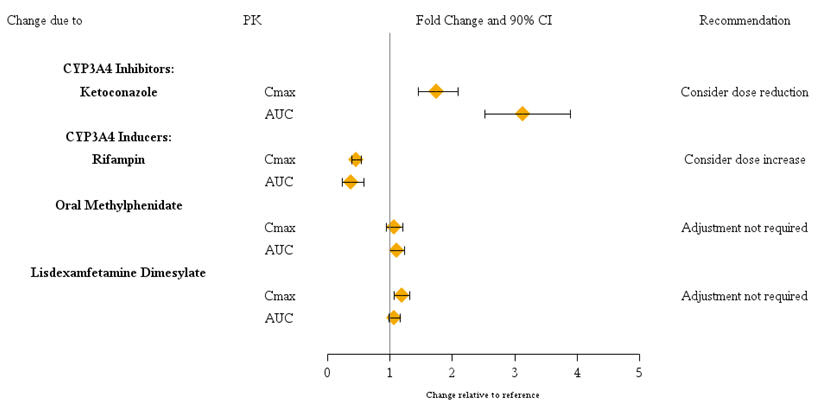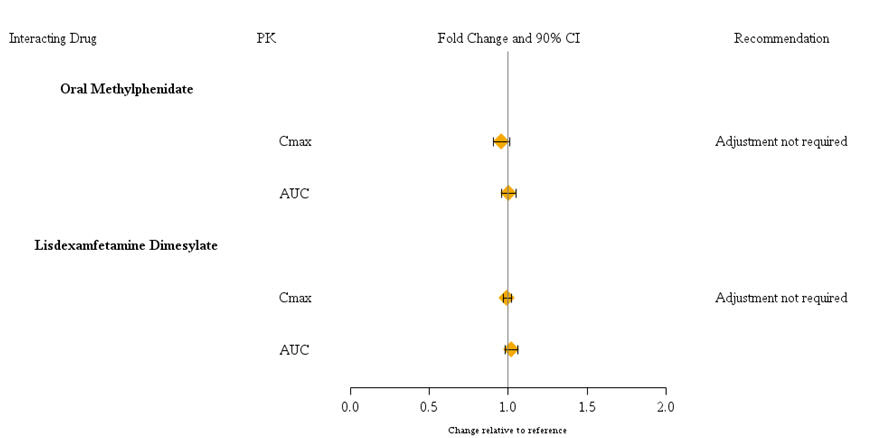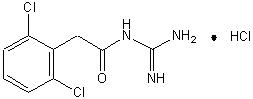 DRUG LABEL: Intuniv
NDC: 64725-0515 | Form: TABLET, EXTENDED RELEASE
Manufacturer: TYA Pharmaceuticals
Category: prescription | Type: HUMAN PRESCRIPTION DRUG LABEL
Date: 20130831

ACTIVE INGREDIENTS: GUANFACINE HYDROCHLORIDE 2 mg/1 1
INACTIVE INGREDIENTS: HYPROMELLOSE 2208 (15000 MPA.S); LACTOSE MONOHYDRATE; POVIDONES; CROSPOVIDONE; METHACRYLIC ACID - METHYL METHACRYLATE COPOLYMER (1:1); CELLULOSE, MICROCRYSTALLINE; GLYCERYL DIBEHENATE; FUMARIC ACID

HIGHLIGHTS OF PRESCRIBING INFORMATION

These highlights do not include all the information needed to use INTUNIV safely and effectively. See full prescribing information for INTUNIV . INTUNIV (guanfacine) extended-release tablets, for oral use Initial U.S. Approval: 1986®®
®

RECENT MAJOR CHANGES

Dosage and Administration, Dose Selection (), 02/2013 2.2

1 INDICATIONS AND USAGE

INTUNIV is a central alpha -adrenergic receptor agonist indicated for the treatment of Attention Deficit Hyperactivity Disorder (ADHD) as monotherapy and as adjunctive therapy to stimulant medications (). ®2A 1

2 DOSAGE AND ADMINISTRATION

- Recommended dose: 1 to 4 mg once daily in the morning or evening (). 2.2
- Begin at a dose of 1 mg once daily and adjust in increments of no more than 1 mg/week (). 2.2
- Do not crush, chew or break tablets before swallowing (). 2.1
- Do not administer with high-fat meals, because of increased exposure (). 2.1
- Do not substitute for immediate-release guanfacine tablets on a mg-per-mg basis, because of differing pharmacokinetic profiles (). 2.3
- If switching from immediate-release guanfacine, discontinue that treatment and titrate with INTUNIV as directed (). ®2.3
- Consider dosing on a mg/kg basis. Improvements observed starting at doses of 0.05-0.08 mg/kg once daily. Doses up to 0.12 mg/kg once daily may provide additional benefit (). 2.2
- When discontinuing, taper the dose in decrements of no more than 1 mg every 3 to 7 days (). 2.5

3 DOSAGE FORMS AND STRENGTHS

Extended-release tablets: 1 mg, 2 mg, 3 mg and 4 mg () 3

4 CONTRAINDICATIONS

History of hypersensitivity to INTUNIV , its inactive ingredients, or other products containing guanfacine ().® 4

5 WARNINGS AND PRECAUTIONS

- Hypotension, bradycardia, and syncope: Use INTUNIV with caution in patients at risk for hypotension, bradycardia, heart block, or syncope (e.g., those taking antihypertensives). Measure heart rate and blood pressure prior to initiation of therapy, following dose increases, and periodically while on therapy. Advise patients to avoid becoming dehydrated or overheated ().® 5.1
- Sedation and somnolence: Occur commonly with INTUNIV . Consider the potential for additive sedative effects with CNS depressant drugs. Caution patients against operating heavy equipment or driving until they know how they respond to INTUNIV (). ®®5.2

6 ADVERSE REACTIONS

Most common adverse reactions (≥5% and at least twice placebo rate) in the monotherapy trials: somnolence, fatigue, nausea, lethargy, and hypotension (). Most common adverse reactions (≥5% and at least twice placebo rate) in the adjunctive trial: somnolence, fatigue, insomnia, dizziness, and abdominal pain (). 66
To report SUSPECTED ADVERSE REACTIONS, contact Shire US Inc. at 1-800-828-2088 or FDA at 1-800-FDA-1088 orwww.fda.gov/medwatch.

7 DRUG INTERACTIONS

- Strong CYP3A4 inhibitors (e.g., ketoconazole): Coadministration increases guanfacine exposure. Guanfacine dose should be limited to no more than 2 mg/day. When discontinuing CYP3A4 inhibitors, guanfacine dose should be doubled based on patient tolerability. The maximum dose should not exceed 4 mg/day (and). 2.77
- Strong CYP3A4 inducers (e.g., rifampin): Coadministration decreases guanfacine exposure. Guanfacine dose may be titrated up to 8 mg/day. When discontinuing CYP3A4 inducers, guanfacine dose should be decreased by half in 1-2 weeks based on patient tolerability. The maximum dose should not exceed 4 mg/day (and). 2.77

8 USE IN SPECIFIC POPULATIONS

Hepatic or Renal Impairment: dose reduction may be required in patients with clinically significant impairment of hepatic or renal function (). 8.6

FULL PRESCRIBING INFORMATION

1 INDICATIONS AND USAGE

INTUNIV is indicated for the treatment of Attention Deficit Hyperactivity Disorder (ADHD) as monotherapy and as adjunctive therapy to stimulant medications. The efficacy of INTUNIV was studied for the treatment of ADHD in three controlled monotherapy clinical trials (up to 8 weeks in duration) and one controlled adjunctive trial with psychostimulants (8 weeks in duration) in children and adolescents ages 6-17 who met DSM-IV criteria for ADHD [ ]. The effectiveness of INTUNIV for longer-term use (more than 8 weeks) has not been systematically evaluated in controlled trials.®®® see Clinical Studies (14)®

2 DOSAGE AND ADMINISTRATION

2.1 General Instruction for Use

Do not administer with high fat meals, due to increased exposure. Swallow tablets whole. Do not crush, chew, or break tablets because this will increase the rate of guanfacine release.

2.2 Dose Selection

INTUNIV should be taken once daily, either in the morning or evening, at approximately same time each day. Begin at a dose of 1 mg/day, and adjust in increments of no more than 1 mg/week. Maintain the dose within the range of 1 mg to 4 mg once daily, depending on clinical response and tolerability, for both monotherapy and adjunctive therapy to a psychostimulant. Doses above 4 mg/day have not been systematically studied in controlled clinical studies . [ ] see Clinical Studies (14.1)

Clinically relevant improvements were observed beginning at doses in the range 0.05-0.08 mg/kg once daily in both mono- and adjunctive therapy. Efficacy increased with increasing weight-adjusted dose (mg/kg). If well tolerated, doses up to 0.12 mg/kg once daily may provide additional benefit.

In clinical trials, there were dose-related and exposure-related risks for several clinically significant adverse reactions (hypotension, bradycardia, sedative events). Thus, consideration should be given to dosing INTUNIV on a mg/kg basis, in order to balance the exposure-related potential benefits and risks of treatment.®

2.3 Switching from Immediate-Release Guanfacine to INTUNIV

If switching from immediate-release guanfacine, discontinue that treatment, and titrate with INTUNIV following above recommended schedule.®

Do not substitute for immediate-release guanfacine tablets on a milligram-per-milligram basis, because of differing pharmacokinetic profiles. INTUNIV has a delayed T , reduced C and lower bioavailability compared to those of the same dose of immediate-release guanfacine .®maxmax [ ] see Clinical Pharmacology (12.3)

2.4 Maintenance Treatment

It is generally agreed that pharmacological treatment of ADHD may be needed for an extended period. The effectiveness of INTUNIV for longer-term use (more than 9 weeks) has not been systematically evaluated in controlled trials. Therefore the physician electing to use INTUNIV for extended periods should periodically re-evaluate the long-term usefulness of the drug for the individual patient.®®

2.5 Discontinuation

Infrequent, transient elevations in blood pressure above original baseline (i.e., rebound) have been reported to occur upon abrupt discontinuation of guanfacine. To minimize these effects, the dose should generally be tapered in decrements of no more than 1 mg every 3 to 7 days.

2.6 Missed Doses

When reinitiating patients to the previous maintenance dose after two or more missed consecutive doses, physicians should consider titration based on patient tolerability.

2.7 Dose Adjustment with Concomitant Use of Strong CYP3A4 Inhibitors or Inducers

Dosage adjustments for INTUNIV are recommended with concomitant use of strong CYP3A4 inhibitors (e.g., boceprevir, clarithromycin, conivaptan, grapefruit juice, indinavir, itraconazole, ketoconazole, lopinavir/ritonavir, mibefradil, nefazodone, nelfinavir, posaconazole, ritonavir, saquinavir, telaprevir, telithromycin, and voriconazole), or CYP3A4 inducers (e.g., avasimibe, carbamazepine, phenytoin, rifampin, and St.John’s wort) (Table 1) .® [] see Drug Interactions (7)

Table 1: Dose Adjustments in Patients Taking Concomitant CYP3A4 Inhibitors or Inducers

Comedications | Scenarios
Comedications | Initiate INTUNIV when taking comedications® | Continue INTUNIV when adding a comedication® | Stop a comedication when continuing INTUNIV ®
Strong CYP3A4 Inhibitors | INTUNIV dose should be limited to 2 mg/day® | INTUNIV dose should be decreased by half.® | INTUNIV dose should be doubled based on patient tolerability. The maximum dose should not exceed 4 mg/day®
Strong CYP3A4 Inducers | INTUNIV dose may be titrated up to 8 mg/day. Consider faster titration (e.g. in increments of 2 mg/week)® | Consider increase INTUNIV dose gradually in 1-2 weeks to 2 fold of the original dose based on patient tolerability. ® | INTUNIV dose should be decreased by half in 1-2 weeks based on patient tolerability. The maximum dose should not exceed 4 mg/day®

3 DOSAGE FORMS AND STRENGTHS

1 mg, 2 mg, 3 mg and 4 mg extended-release tablets

4 CONTRAINDICATIONS

Patients with a history of hypersensitivity to INTUNIV , its inactive ingredients or other products containing guanfacine should not take INTUNIV .® [ ] see Description (11)®

5 WARNINGS AND PRECAUTIONS

5.1 Hypotension, Bradycardia, and Syncope

Treatment with INTUNIV can cause dose-dependent decreases in blood pressure and heart rate. Decreases were less pronounced over time of treatment. Orthostatic hypotension and syncope have been reported .® [] see Adverse Reactions (6.1)

Measure heart rate and blood pressure prior to initiation of therapy, following dose increases, and periodically while on therapy. Use INTUNIV with caution in patients with a history of hypotension, heart block, bradycardia, cardiovascular disease, or who have a history of syncope or may have a condition that predisposes them to syncope, such as hypotension, orthostatic hypotension, bradycardia, or dehydration. Use INTUNIV with caution in patients treated concomitantly with antihypertensives or other drugs that can reduce blood pressure or heart rate or increase the risk of syncope. Advise patients to avoid becoming dehydrated or overheated.®®

5.2 Sedation and Somnolence

Somnolence and sedation were commonly reported adverse reactions in clinical studies [ . Before using INTUNIV with other centrally active depressants (such as phenothiazines, barbiturates, or benzodiazepines), consider the potential for additive sedative effects. Caution patients against operating heavy equipment or driving until they know how they respond to treatment with INTUNIV Advise patients to avoid use with alcohol. ] see Adverse Reactions (6.1)®®.

6 ADVERSE REACTIONS

The following serious adverse reactions are described elsewhere in the labelling:

- Hypotension, bradycardia, and syncope [ ] see Warnings and Precautions (5.1)
- Sedation and somnolence [ ] see Warnings and Precautions (5.2)

6.1 Clinical Trials Experience

Because clinical trials are conducted under widely varying conditions, adverse reaction rates observed in the clinical trials of a drug cannot be directly compared to rates in the clinical trials of another drug and may not reflect the rates observed in clinical practice.

A total of 2,028 subjects have been exposed to INTUNIV while participating in clinical trials. This includes 1,533 patients from completed studies in children and adolescents, and 495 subjects in completed studies in adult healthy volunteers.®

The mean duration of exposure of 446 patients that previously participated in two 2-year, open-label long-term studies was approximately 10 months.

Monotherapy Trials

The most commonly observed adverse reactions (incidence ≥ 5% and at least twice the rate for placebo) in the monotherapy trials (Studies 1 and 2) with INTUNIV were: somnolence, fatigue, nausea, lethargy, and hypotension. Most Common Adverse Reactions -®

Twelve percent (12%) of patients receiving INTUNIV discontinued from the monotherapy clinical studies (Studies 1 and 2) due to adverse reactions, compared to 4% in the placebo group. The most common adverse reactions leading to discontinuation of INTUNIV -treated patients from the studies were somnolence/sedation (6%) and fatigue (2%). Less common adverse reactions leading to discontinuation (occurring in approximately 1% of patients) included: hypotension, headache, and dizziness. Adverse Reactions Leading to Discontinuation -®®

Adjunctive Trial

The most commonly observed adverse reactions (incidence ≥ 5% and at least twice the rate for placebo) in the adjunctive trial with INTUNIV were: somnolence, fatigue, insomnia, dizziness, and abdominal pain. Most Common Adverse Reactions -®

In the adjunctive clinical study, 3% of patients receiving INTUNIV discontinued due to adverse reactions, compared to 1% in the placebo group. Each adverse reaction leading to discontinuation occurred in less than 1% of INTUNIV -treated patients. Adverse Reactions Leading to Discontinuation –®®

Short Term Monotherapy Clinical Studies

- Two short-term, placebo-controlled, double-blind pivotal studies (Studies 1 and 2) were conducted in children and adolescents with ADHD, using fixed doses of INTUNIV (1 mg, 2 mg, 3 mg, and 4 mg/day). The most commonly reported adverse reactions (occurring in ≥ 2% of patients) that were considered drug-related and reported in a greater percentage of patients taking INTUNIV compared to patients taking placebo are shown in Table 2. Adverse reactions that were dose-related include: somnolence/sedation, abdominal pain, dizziness, hypotension, dry mouth and constipation. Common Adverse Reactions®®

Table 2: Percentage of Patients Experiencing Common (≥ 2%) Adverse Reactions in Short-Term
Monotherapy Studies 1 and 2
Adverse Reaction Term | All Doses of INTUNIV (N=513) ® | Placebo (N=149)
Somnolencea | 38% | 12%
Headache | 24% | 19%
Fatigue | 14% | 3%
Abdominal painb | 11% | 9%
Hypotensionc | 7% | 3%
Nausea | 6% | 2%
Lethargy | 6% | 3%
Dizziness | 6% | 4%
Irritability | 6% | 4%
Decreased appetite | 5% | 3%
Dry mouth | 4% | 1%
Constipation | 3% | 1%
a: The somnolence term includes somnolence, sedation, and hypersomnia. b: The abdominal pain term includes abdominal pain, abdominal pain upper, and abdominal pain lower. c: The hypotension term includes hypotension, orthostatic hypotension, and decreased blood pressure.

In an 8-week, placebo-controlled study in children 6-12 years of age with ADHD in which INTUNIV was dosed once (1-4 mg/day) in the morning or evening (Study 4), the safety profile was consistent with the once daily morning dosing of INTUNIV .®®

Short Term Adjunctive Clinical Study

- A 8-week, placebo-controlled, double-blind, dose-optimized pivotal study (Study 3) was conducted in children and adolescents aged 6-17 years with a diagnosis of ADHD who were identified as having a sub-optimal response to psychostimulants. Patients received INTUNIV (1 mg, 2 mg, 3 mg, and 4 mg/day) or placebo, dosed in the morning or in the evening, in combination with their morning dose of psychostimulant. The most commonly reported adverse reactions (occurring in ≥ 2% of patients in the overall INTUNIV group) that were reported in a greater percentage of patients taking INTUNIV compared to patients taking placebo are shown in Table 3. Common Adverse Reactions®®®

Table 3: Percentage of Patients Experiencing Common (≥ 2%) Adverse Reactions in Short-Term Adjunctive Study 3
Adverse Reaction Term | All Doses of INTUNIV® (N=302)a | Placebo (N=153)
Headache | 21% | 13%
Somnolenceb | 18% | 7%
Insomniac | 12% | 6%
Fatigue | 10% | 3%
Abdominal paind | 10% | 3%
Dizziness | 8% | 4%
Decreased appetite | 7% | 4%
Nausea | 5% | 3%
Diarrhea | 4% | 1%
Hypotensione | 3% | 0%
Affect lability | 2% | 1%
Bradycardia | 2% | 0%
Constipation | 2% | 0%
Dry mouth | 2% | 0%
a: The morning and evening dose groups of INTUNIV are combined. b: The somnolence term includes somnolence, sedation, and hypersomnia. c: The insomnia term includes insomnia, initial insomnia, and middle insomnia. d: The abdominal pain term includes abdominal pain, abdominal pain upper, and abdominal pain lower. e: The hypotension term includes hypotension, orthostatic hypotension, and decreased blood pressure.®

Effects on Blood Pressure and Heart Rate

In the monotherapy pediatric, short-term, controlled trials (Studies 1 and 2), the maximum mean changes from baseline in systolic blood pressure, diastolic blood pressure, and pulse were −5 mmHg, −3 mmHg, and −6 bpm, respectively, for all dose groups combined (generally one week after reaching target doses of 1 mg/day, 2 mg/day, 3 mg/day or 4 mg/day). These changes were dose dependent. Decreases in blood pressure and heart rate were usually modest and asymptomatic; however, hypotension and bradycardia can occur. Hypotension was reported as an adverse reaction for 7% of the INTUNIV group and 3% of the placebo group. This includes orthostatic hypotension, which was reported for 1% of the INTUNIV group and none in the placebo group. In the adjunctive trial, hypotension (3%) and bradycardia (2%) were observed in patients treated with INTUNIV as compared to none in the placebo group. In long-term, open label studies, (mean exposure of approximately 10 months), maximum decreases in systolic and diastolic blood pressure occurred in the first month of therapy. Decreases were less pronounced over time. Syncope occurred in 1% of pediatric subjects in the clinical program. The majority of these cases occurred in the long-term, open-label studies.®®®

Other Adverse Reactions Observed in Clinical Studies

Table 4 includes additional adverse reactions observed in short-term, placebo-controlled and long-term, open-label clinical studies not included elsewhere in section 6.1, listed by organ system.

Table 4: Other adverse reactions observed in clinical studies
Body System | Adverse Reaction
Cardiac | Atrioventricular block, sinus arrhythmia
Gastrointestinal | Dyspepsia, stomach discomfort, vomiting
General | Asthenia, chest pain
Immune System Disorders | Hypersensitivity
Investigations | Increased alanine amino transferase, increased weight
Nervous system | Convulsion
Psychiatric | Agitation, anxiety, depression, nightmare
Renal | Increased urinary frequency, enuresis
Respiratory | Asthma
Vascular | Hypertension, pallor

6.2 Post-marketing Experience

The following adverse reactions have been identified during post-approval use of guanfacine. Because these reactions are reported voluntarily from a population of uncertain size, it is not always possible to reliably estimate their frequency or establish a causal relationship to drug exposure.

An open-label post-marketing study involving 21,718 patients was conducted to assess the safety of guanfacine (as the hydrochloride) 1 mg/day given at bedtime for 28 days. Guanfacine was administered with or without other antihypertensive agents. Adverse events reported in the post-marketing study at an incidence greater than 1% included dry mouth, dizziness, somnolence, fatigue, headache and nausea. The most commonly reported adverse events in this study were the same as those observed in controlled clinical trials.

Less frequent, possibly guanfacine-related events observed in the post-marketing study and/or reported spontaneously, not included in , include: section 6.1

edema, malaise, tremor General:

palpitations, tachycardia Cardiovascular:

paresthesias, vertigo Central Nervous System:

blurred vision Eye Disorders:

arthralgia, leg cramps, leg pain, myalgia Musculo-Skeletal System:

confusion, hallucinations Psychiatric:

impotence Reproductive System, Male:

dyspnea Respiratory System:

alopecia, dermatitis, exfoliative dermatitis, pruritus, rash Skin and Appendages:

alterations in taste Special Senses:

7 DRUG INTERACTIONS

Guanfacine is primarily metabolized by CYP3A4 and its plasma concentrations can be affected significantly by CYP3A4 inhibitors or inducers (Figure 1). Dose adjustments are recommended . Guanfacine does not significantly affect exposures of methylphenidate and lisdexamfetamine when coadministered (Figure 2). Therefore, no dose adjustments in methylphenidate or lisdexamfetamine are necessary. [] see Dosage and Administration (2.7)

Figure 1: Impact of Other Drugs on the Pharmacokinetics (PK) of Intuniv

Figure 2: Impact of Intuniv on the Pharmacokinetics (PK) of Other Drugs

8 USE IN SPECIFIC POPULATIONS

8.1 Pregnancy

Pregnancy Category B

Risk Summary

There are no adequate and well-controlled studies of INTUNIV in pregnant women. No fetal harm was observed in rats and rabbits with administration of guanfacine at 6 and 4 times, respectively, the maximum recommended human dose. Because animal studies are not always predictive of human response, this drug should be used during pregnancy only if clearly needed.

Animal data

Reproduction studies conducted in rats have shown that guanfacine crosses the placenta. However, administration of guanfacine to rats and rabbits at 6 and 4 times, respectively, the maximum recommended human dose of 4 mg/day on a mg/m basis resulted in no evidence of harm to the fetus. Higher doses (20 times the maximum recommended human dose in both rabbits and rats) were associated with reduced fetal survival and maternal toxicity.^2

8.3 Nursing Mothers

It is not known whether guanfacine is excreted in human milk; however, guanfacine is excreted in rat milk. Because many drugs are excreted in human milk, caution should be exercised when INTUNIV is administered to a nursing woman. Observe human milk-fed infants for sedation and somnolence.®

8.4 Pediatric Use

Safety and efficacy of INTUNIV in pediatric patients less than 6 years of age have not been established. ®

Animal Data

In studies in juvenile rats, guanfacine alone produced a slight delay in sexual maturation in males and females at 2-3 times the maximum recommended human dose (MRHD). Guanfacine in combination with methylphenidate produced a slight delay in sexual maturation and decreased growth as measured by a decrease in bone length in males at a dose of guanfacine comparable to the MRHD and a dose of methylphenidate approximately 4 times the MRHD.

In a study where juvenile rats were treated with guanfacine alone from 7 to 59 days of age, development was delayed as indicated by a slight delay in sexual maturation and decreased body weight gain in males at 2 mg/kg/day and in females at 3 mg/kg/day. The No Adverse Effect Level (NOAEL) for delayed sexual maturation was 1 mg/kg/day, which is equivalent to the MRHD of 4 mg/day, on a mg/m basis. The effects on fertility were not evaluated in this study.^2

In a study where juvenile rats were treated with guanfacine in combination with methylphenidate from 7 to 59 days of age, a decrease in ulna bone length and a slight delay in sexual maturation were observed in males given 1 mg/kg/day of guanfacine in combination with 50 mg/kg/day of methylphenidate. The NOAELs for these findings were 0.3 mg/kg of guanfacine in combination with 16 mg/kg/day of methylphenidate, which are equivalent to 0.3 and 1.4 times the MRHD of 4 mg/day and 54 mg/day for guanfacine and methylphenidate, respectively, on a mg/m basis. These findings were not observed with guanfacine alone at 1 mg/kg/day or methylphenidate alone at 50 mg/kg/day.^2

8.5 Geriatric Use

The safety and efficacy of INTUNIV in geriatric patients have not been established.®

8.6 Use in Patients with Renal or Hepatic Impairment

Renal Impairment

The impact of renal impairment on the pharmacokinetics of guanfacine in children was not assessed. In adult patients with impaired renal function, the cumulative urinary excretion of guanfacine and the renal clearance diminished as renal function decreased. In patients on hemodialysis, the dialysis clearance was about 15% of the total clearance. The low dialysis clearance suggests that the hepatic elimination (metabolism) increases as renal function decreases. It may be necessary to adjust the dose in patients with significant impairment of renal function.

Hepatic Impairment

The impact of hepatic impairment on PK of guanfacine in children was not assessed. Guanfacine in adults is cleared both by the liver and the kidney, and approximately 50% of the clearance of guanfacine is hepatic. It may be necessary to adjust the dose in patients with significant impairment of hepatic function.

9 DRUG ABUSE AND DEPENDENCE

9.1 Controlled Substance

INTUNIV is not a controlled substance and has no known potential for abuse or dependence.®

10 OVERDOSAGE

Symptoms

Post-marketing reports of guanfacine overdosage indicate that hypotension, drowsiness, lethargy, and bradycardia have been observed following overdose. Initial hypertension may develop early and may be followed by hypotension. Similar symptoms have been described in voluntary reports to the American Association of Poison Control Center’s National Poison Data System. Miosis of the pupils may be noted on examination No fatal overdoses of guanfacine have been reported in published literature. .

Treatment

Consult a Certified Poison Control Center by calling 1-800-222-1222 for up to date guidance and advice.

Management of INTUNIV overdose should include monitoring for and the treatment of initial hypertension, if that occurs, as well as hypotension, bradycardia, lethargy and respiratory depression. Children and adolescents who develop lethargy should be observed for the development of more serious toxicity including coma, bradycardia and hypotension for up to 24 hours, due to the possibility of delayed onset hypotension.®

11 DESCRIPTION

INTUNIV is a once-daily, extended-release formulation of guanfacine hydrochloride (HCl) in a matrix tablet formulation for oral administration only. The chemical designation is N-amidino-2-(2,6-dichlorophenyl) acetamide monohydrochloride. The molecular formula is C H Cl N O·HCl corresponding to a molecular weight of 282.55. The chemical structure is:®9923

Guanfacine HCl is a white to off-white crystalline powder, sparingly soluble in water (approximately 1 mg/mL) and alcohol and slightly soluble in acetone. The only organic solvent in which it has relatively high solubility is methanol (>30 mg/mL). Each tablet contains guanfacine HCl equivalent to 1 mg, 2 mg, 3 mg, or 4 mg of guanfacine base. The tablets also contain hypromellose, methacrylic acid copolymer, lactose, povidone, crospovidone, microcrystalline cellulose, fumaric acid, and glyceryl behenate. In addition, the 3mg and 4mg tablets also contain green pigment blend PB-1763.

12 CLINICAL PHARMACOLOGY

12.1 Mechanism of Action

Guanfacine is a central alpha -adrenergic receptor agonist. Guanfacine is not a central nervous system (CNS) stimulant. The mechanism of action of guanfacine in ADHD is not known.2A

12.2 Pharmacodynamics

Guanfacine is a selective central alpha -adrenergic receptor agonist in that it has a 15-20 times higher affinity for this receptor subtype than for the alpha or alpha subtypes.2A2B2C

Guanfacine is a known antihypertensive agent. By stimulating central alpha -adrenergic receptors, guanfacine reduces sympathetic nerve impulses from the vasomotor center to the heart and blood vessels. This results in a decrease in peripheral vascular resistance and a reduction in heart rate.2A

Effects on Height, Weight, and Body Mass Index (BMI)

Patients taking INTUNIV demonstrated similar growth compared to normative data. Patients taking INTUNIV had a mean increase in weight of 0.5 kg (1 lb) compared to those receiving placebo over a comparative treatment period. Patients receiving INTUNIV for at least 12 months in open-label studies gained an average of 8 kg (17 lbs) in weight and 8 cm (3 in) in height. The height, weight, and BMI percentile remained stable in patients at 12 months in the long-term studies compared to when they began receiving INTUNIV . ®®®®

Effect on ECG

The effect of two dose levels of immediate-release guanfacine (4 mg and 8 mg) on the QT interval was evaluated in a double-blind, randomized, placebo- and active-controlled, cross-over study in healthy adults. A dose-dependent decrease in heart rate was observed during the first 12 hours, at time of maximal concentrations. The mean change in heart rate was -13 bpm at 4 mg and -22 bpm at 8 mg. An apparent increase in mean QTc was observed for both doses. However, guanfacine does not appear to interfere with cardiac repolarization of the form associated with pro-arrhythmic drugs. This finding has no known clinical relevance.

12.3 Pharmacokinetics

Absorption and Distribution

Guanfacine is readily absorbed and approximately 70% bound to plasma proteins independent of drug concentration. After oral administration of INTUNIV the time to peak plasma concentration is approximately 5 hours in children and adolescents with ADHD.®

Immediate-release guanfacine and INTUNIV have different pharmacokinetic characteristics; dose substitution on a milligram for milligram basis will result in differences in exposure.®

A comparison across studies suggests that the C is 60% lower and AUC 43% lower, respectively, for INTUNIV compared to immediate-release guanfacine. Therefore, the relative bioavailability of INTUNIV to immediate-release guanfacine is 58%. The mean pharmacokinetic parameters in adults following the administration of INTUNIV 1 mg once daily and immediate-release guanfacine 1mg once daily are summarized in Table 5.max0-∞®®®

Table 5: Pharmacokinetic Parameters in Adults
Parameter | INTUNIV® 1 mg once daily (n=52) | Immediate-release guanfacine 1 mg once daily (n=12)
C (ng/mL) max | 1.0 ± 0.3 | 2.5 ± 0.6
AUC (ng.h/mL) 0-∞ | 32 ± 9 | 56 ± 15
t (h) max | 6.0 (4.0 - 8.0) | 3.0 (1.5-4.0)
t (h) 1/2 | 18 ± 4 | 16 ± 3

Note: Values are mean +/- SD, except for t which is median (range) max

Exposure to guanfacine was higher in children (ages 6-12) compared to adolescents (ages 13-17) and adults. After oral administration of multiple doses of INTUNIV 4 mg, the C was 10 ng/mL compared to 7 ng/mL and the AUC was 162 ng h/mL compared to 116 ng h/mL in children (ages 6-12) and adolescents (ages 13-17), respectively. These differences are probably attributable to the lower body weight of children compared to adolescents and adults.®max

The pharmacokinetics were affected by intake of food when a single dose of INTUNIV 4 mg was administered with a high-fat breakfast. The mean exposure increased (C ~75% and AUC ~40%) compared to dosing in a fasted state.®max

Dose Proportionality

Following administration of INTUNIV in single doses of 1 mg, 2 mg, 3 mg, and 4 mg to adults, C and AUC of guanfacine were proportional to dose.®max0-∞

Metabolism and Elimination

In vitro studies with human liver microsomes and recombinant CYP’s demonstrated that guanfacine was primarily metabolized by CYP3A4. In pooled human hepatic microsomes, guanfacine did not inhibit the activities of the major cytochrome P450 isoenzymes (CYP1A2, CYP2C8, CYP2C9, CYP2C19, CYP2D6 or CYP3A4/5). Guanfacine is a substrate of CYP3A4/5 and exposure is affected by CYP3A4/5 inducers/inhibitors.

Renal and Hepatic Impairment

The impact of renal impairment on PK of guanfacine in children was not assessed . [] see Use in Specific Populations (8.6)

13 NONCLINICAL TOXICOLOGY

13.1 Carcinogenesis, Mutagenesis, Impairment of Fertility

Carcinogenesis No carcinogenic effect of guanfacine was observed in studies of 78 weeks in mice or 102 weeks in rats at doses up to 6-7 times the maximum recommended human dose of 4 mg/day on a mg/ m basis.
^2

Mutagenesis Guanfacine was not genotoxic in a variety of test models, including the Ames test and an chromosomal aberration test; however, a marginal increase in numerical aberrations (polyploidy) was observed in the latter study.
in vitro

Impairment of Fertility No adverse effects were observed in fertility studies in male and female rats at doses up to 30 times the maximum recommended human dose on a mg/ m basis.
^2

14 CLINICAL STUDIES

14.1 Safety and Efficacy Studies

The efficacy of INTUNIV in the treatment of ADHD was established in 3 placebo-controlled monotherapy trials (Studies 1, 2, and 4) and in 1 placebo-controlled adjunctive trial with psychostimulants (Study 3) in pediatric population. Studies 1, 2, and 3 were conducted in children and adolescents ages 6-17 and Study 4 was conducted in children ages 6-12 years.®

Studies 1 and 2: Fixed-dose INTUNIV Monotherapy®

Study 1 was a double-blind, placebo-controlled, parallel-group, fixed dose study, in which efficacy of once daily dosing with INTUNIV (2 mg, 3 mg and 4 mg) was evaluated for 5 weeks (n=345). Study 2 was a double-blind, placebo-controlled, parallel-group, fixed-dose study, in which efficacy of once daily dosing with INTUNIV (1 mg, 2 mg, 3 mg and 4 mg) was evaluated for 6 weeks (n=324). In both studies, randomized subjects in 2 mg, 3 mg and 4 mg dose groups were titrated to their target fixed dose, and continued on the same dose until a dose tapering phase started The lowest dose of 1 mg used in Study 2 was assigned only to patients less than 50 kg (110 lbs). Patients who weighed less than 25 kg (55 lbs) were not included in either study.®®

Signs and symptoms of ADHD were evaluated on a once weekly basis using the clinician administered and scored ADHD Rating Scale (ADHD-RS-IV), which includes both hyperactive/impulsive and inattentive subscales. The primary efficacy outcome was the change from baseline to endpoint in ADHD-RS-IV total scores. Endpoint was defined as the last post-randomization treatment week for which a valid score was obtained prior to dose tapering (up to Week 5 in Study 1 and up to Week 6 in Study 2).

The mean reductions in ADHD-RS-IV total scores at endpoint were statistically significantly greater for INTUNIV compared to placebo for Studies 1 and 2. Placebo-adjusted changes from baseline were statistically significant for each of the 2 mg, 3 mg, and 4 mg INTUNIV randomized treatment groups in both studies, as well as the 1 mg INTUNIV treatment group (for patients 55-110 lbs) that was included only in Study 2 (see Table 6). ®®®

Dose-responsive efficacy was evident, particularly when data were examined on a weight-adjusted (mg/kg) basis. When evaluated over the dose range of 0.01-0.17 mg/kg/day, clinically relevant improvements were observed beginning at doses in the range 0.05-0.08 mg/kg/day. Doses up to 0.12 mg/kg/day were shown to provide additional benefit.

Controlled, monotherapy long-term efficacy studies (>9 weeks) have not been conducted.

In the monotherapy trials (Studies 1 and 2), subgroup analyses were performed to identify any differences in response based on gender or age (6-12 vs. 13-17). Analyses of the primary outcome did not suggest any differential responsiveness on the basis of gender. Analyses by age revealed a statistically significant treatment effect only in the 6-12 age subgroup. Due to the relatively small proportion of adolescent patients (ages 13-17) enrolled into these studies (approximately 25%), these data may not be sufficient to demonstrate efficacy in the adolescent patients. In these studies, patients were randomized to a fixed dose of INTUNIV rather than optimized by body weight. Therefore, some adolescent patients were randomized to a dose that might have resulted in relatively lower plasma guanfacine concentrations compared to the younger patients. Over half (55%) of the adolescent patients received doses of 0.01-0.04mg/kg. In studies in which systematic pharmacokinetic data were obtained, there was a strong inverse correlation between body weight and plasma guanfacine concentrations.®

Table 6: Fixed dose Studies

Study; (Age Range) | Primary Efficacy Measure | Treatment Group
Study; (Age Range) | Primary Efficacy Measure | Placebo | Intuniv® 1mg | Intuniv® 2mg | Intuniv® 3mg | Intuniv® 4mg
(6 – 17 years); 1 | Mean Baseline (SD) | 38.1 (9.34) | -- | 36.1 (9.99) | 36.8 (8.72) | 38.4 (9.21)
(6 – 17 years); 1 | LS Mean Change from Baseline (SE) | -8.5 (1.42) | -- | -15.9 (1.37) | -16.0 (1.38) | -18.5 (1.39)
(6 – 17 years); 1 | LS Mean Difference from Placebo (95% CI) | -- | -- | -7.4 (-11.3, -3.5) a | -7.5 (-11.4, -3.6) a | -10.0 (-13.9, -6.1) a
(6 – 17 years); 2 | Mean Baseline (SD) | 39.3 (8.85) | 41.7 (7.81) | 39.9 (8.74) | 39.1 (9.22) | 40.6 (8.57)
(6 – 17 years); 2 | LS Mean Change from Baseline (SE) | -12.7 (1.60) | -19.4 (1.69) | -18.1 (1.60) | -20.0 (1.64) | -20.6 (1.60)
(6 – 17 years); 2 | LS Mean Difference from Placebo (95% CI) | -- | -6.8 (-11.3, -2.2) a | -5.4 (-9.9, -0.9) a | -7.3 (-11.8, -2.8) a | -7.9 (-12.3, -3.4) a

LS Mean: least-square mean; SD: standard deviation; SE: standard error; 95% CI (unadjusted) Doses were shown to be statistically significantly superior to placebo.
a
Study 3: Flexible-dose INTUNIV as Adjunctive Therapy to Psychostimulants®

Study 3 was a double-blind, randomized, placebo-controlled, dose-optimization study, in which efficacy of once daily optimized dosing (morning or evening) with INTUNIV (1mg, 2mg, 3mg and 4mg), when co-administered with psychostimulants, was evaluated for 8 weeks, in children and adolescents aged 6-17 years with a diagnosis of ADHD, with a sub-optimal response to stimulants (n=455). Subjects were started at the 1 mg INTUNIV dose level and were titrated weekly over a 5-week dose-optimization period to an optimal INTUNIV dose not to exceed 4 mg/day based on tolerability and clinical response. The dose was then maintained for a 3-week dose maintenance period before entry to 1 week of dose tapering. Subjects took INTUNIV either in the morning or the evening while maintaining their current dose of psychostimulant treatment given each morning. Allowable psychostimulants in the study were ADDERALL XR , VYVANSE , CONCERTA , FOCALIN XR , RITALIN LA , METADATE CD or FDA-approved generic equivalents.®®®®®®®®®®

Symptoms of ADHD were evaluated on a weekly basis by clinicians using the ADHD Rating Scale (ADHD-RS-IV), which includes both hyperactive/impulsive and inattentive subscales. The primary efficacy outcome was the change from baseline to endpoint in ADHD-RS-IV total scores. Endpoint was defined as the last post-randomization treatment week prior to dose tapering for which a valid score was obtained (up to Week 8).

Mean reductions in ADHD-RS-IV total scores at endpoint were statistically significantly greater for INTUNIV given in combination with a psychostimulant compared to placebo given with a psychostimulant for Study 3, for both morning and evening INTUNIV dosing (see Table 7). Nearly two-thirds (64.2%) of subjects reached optimal doses in the 0.05-0.12 mg/kg/day range.®®

Study 4: Flexible-dose INTUNIV Monotherapy®

Study 4 was a double-blind, randomized, placebo-controlled, dose-optimization study, in which efficacy of once daily dosing (morning or evening) with INTUNIV (1mg, 2mg, 3mg, and 4mg) was evaluated for 8 weeks in children aged 6-12 years (n=340).®

Signs and symptoms of ADHD were evaluated on a once weekly basis using the clinician administered and scored ADHD Rating Scale (ADHD-RS-IV), which includes both hyperactive/impulsive and inattentive subscales. The primary efficacy outcome was the change from baseline score at endpoint on the ADHD-RS-IV total scores. Endpoint was defined as the last post-randomization treatment week for which a valid score was obtained prior to dose tapering (up to Week 8).

Mean reductions in ADHD-RS-IV total scores at endpoint were statistically significantly greater for INTUNIV compared to placebo in both AM and PM dosing groups of INTUNIV (see Table 7).®®
Table 7: Flexible-Dose studies

Study (Age Range) |  | Treatment Group
Study (Age Range) |  | Placebo | Intuniv® 1mg – 4mg
 |  |  | AM | PM
(6 – 17 years); 3 a | Mean Baseline (SD) | 37.7 (7.75) | 37.6 (8.13) | 37.0 (7.65)
(6 – 17 years); 3 a | LS Mean Change from Baseline (SE) | -15.9 (0.96) | -20.3 (0.97) | -21.2 (0.97)
(6 – 17 years); 3 a | LS Mean Difference from Placebo (95% CI) | -- | -4.5 (-7.5, -1.4)b | -5.3 (-8.3, -2.3)b
(6 – 12 years); 4 | Mean Baseline (SD) | 42.9 (6.21) | 41.7 (6.39) | 41.6 (6.66)
(6 – 12 years); 4 | LS Mean Change from Baseline (SE) | -10.6 (1.20) | -20.0 (1.23) | -20.4 (1.19)
(6 – 12 years); 4 | LS Mean Difference from Placebo (95% CI) | -- | -9.4 (-12.8, -6.0)b | -9.8 (-13.1, -6.4)b

LS Mean: least-square mean; SD: standard deviation; SE: standard error; 95% CI (unadjusted) Treatment was given in combination with a psychostimulant. Doses were shown to be statistically significantly superior to placebo.
a
b

16 HOW SUPPLIED/STORAGE AND HANDLING

NDC:64725-0515-1 in a CONTAINER of 30 TABLET, EXTENDED RELEASES

17 PATIENT COUNSELING INFORMATION

See FDA-approved patient labeling (Patient Information)

Dosing and Administration

Instruct patients to swallow INTUNIV whole with water, milk or other liquid. Patients should not take INTUNIV together with a high-fat meal, since this can raise blood levels of INTUNIV . Instruct the parent or caregiver to supervise the child or adolescent taking INTUNIV and to keep the bottle of tablets out of reach of children.® Tablets should not be crushed, chewed or broken prior to administration because this may increase the rate of release of the active drug .®®®

Instruct patients on how to properly taper the medication, if the physician decides to discontinue treatment. [ ]. see Dosage and Administration (2.5)

Adverse Reactions

Advise patients that sedation can occur, particularly early in treatment or with dose increases. Caution against operating heavy equipment or driving until they know how they respond to treatment with INTUNIV Headache and abdominal pain can also occur. If any of these symptoms persist, or other symptoms occur, the patient should be advised to discuss the symptoms with the physician.® [ ]. see Warnings and Precautions (5.2)

Advise patients to avoid becoming dehydrated or overheated, which may potentially increase the risks of hypotension and syncope Advise patients to avoid use with alcohol. [ ]. see Warnings and Precautions (5.1)

Patient Information INTUNIV (
® in-TOO-niv)
(guanfacine)
Extended-Release Tablets

Read the Patient Information that comes with INTUNIV before you start taking it and each time you get a refill. There may be new information.® This leaflet does not take the place of talking with your doctor about your medical condition or your treatment.

What is INTUNIV ?®

INTUNIV is a prescription medicine used to treat the symptoms of attention deficit/hyperactivity disorder (ADHD).®

INTUNIV is not a central nervous system (CNS) stimulant.®

What should I tell my doctor before taking INTUNIV ?®

Before you take INTUNIV , tell your doctor if you: ®

- have heart problems or a low heart rate
- have fainted
- have low blood pressure
- have liver or kidney problems
- have any other medical conditions
- are pregnant or plan to become pregnant. It is not known if INTUNIV will harm your unborn baby. Talk to your doctor if you are pregnant or plan to become pregnant. ®
- are breast-feeding or plan to breast-feed. It is not known if INTUNIV passes into your breast milk. Talk to your doctor about the best way to feed your baby while taking INTUNIV .®®

Tell your doctor about all of the medicines you take, including prescription and non-prescription medicines, vitamins, and herbal supplements.

INTUNIV may affect the way other medicines work, and other medicines may affect how INTUNIV works.®®

Especially tell your doctor if you take:

- ketoconazole
- medicines that can affect enzyme metabolism
- high blood pressure medicine
- sedatives
- benzodiazepines
- barbiturates
- antipsychotics

Ask your doctor or pharmacist for a list of these medicines, if you are not sure.

Know the medicines you take. Keep a list of them and show it to your doctor and pharmacist when you get a new medicine.

How should I take INTUNIV ? ®

- Take INTUNIV exactly as your doctor tells you. ®
- Your doctor may change your dose. Do not change your dose of INTUNIV without talking to your doctor. ®
- Do not stop taking INTUNIV without talking to your doctor. ®
- INTUNIV should be taken 1 time a day in the morning or in the evening, either alone or in combination with an ADHD stimulant medication that your doctor may prescribe. Your doctor will tell you when to take INTUNIV and when to take your ADHD stimulant medication. ®®
- INTUNIV should be swallowed whole with a small amount of water, milk, or other liquid. ®
- Do not crush, chew, or break INTUNIV . Tell your doctor if you can not swallow INTUNIV whole. ®®
- Do not take INTUNIV with a high-fat meal. ®
- Your doctor will check your blood pressure and heart rate while you take INTUNIV . ®
- If you take too much INTUNIV , call your local Poison Control Center or go to the nearest emergency room right away.®

What should I avoid while taking INTUNIV ? ®

- Do not drive, operate heavy machinery, or do other dangerous activities until you know how INTUNIV affects you. INTUNIV can slow your thinking and motor skills. ®®
- Do not drink alcohol or take other medicines that make you sleepy or dizzy while taking INTUNIV until you talk with your doctor. INTUNIV taken with alcohol or medicines that cause sleepiness or dizziness may make your sleepiness or dizziness worse.®®

What are the possible side effects of INTUNIV ?®

INTUNIV may cause serious side effects including:®

- low blood pressure
- low heart rate
- fainting
- sleepiness

Get medical help right away, if you have any of the symptoms listed above.
The most common side effects of INTUNIV include:®

- sleepiness
- tiredness
- trouble sleeping
- low blood pressure
- nausea
- stomach pain
- dizziness

Tell the doctor if you have any side effect that bothers you or that does not go away.

These are not all the possible side effects of INTUNIV . For more information, ask your doctor or pharmacist.®

Call your doctor for medical advice about side effects. You may report side effects to FDA at 1-800-FDA-1088.

How should I store INTUNIV ? ®

- Store INTUNIV between 59 F to 86 F (15 C to 30 C)®oooo

Keep INTUNIV and all medicines out of the reach of children.®

General Information about INTUNIV®

Medicines are sometimes prescribed for purposes other than those listed in a Patient Information Leaflet. Do not use INTUNIV for a condition for which it was not prescribed. Do not give INTUNIV to other people, even if they have the same symptoms that you have. It may harm them.®®

This leaflet summarizes the most important information about INTUNIV . If you would like more information, talk with your doctor. You can ask your pharmacist or doctor for information about INTUNIV that is written for health professionals. For more information, go to®®
www.INTUNIV.comor call 1-800-828-2088.

What are the ingredients in INTUNIV ?®

guanfacine hydrochloride Active ingredient:

hypromellose, methacrylic acid copolymer, lactose, povidone, crospovidone, microcrystalline cellulose, fumaric acid, and glycerol behenate. In addition, the 3mg and 4mg tablets also contain green pigment blend PB-1763. Inactive ingredients:

Manufactured for Shire US Inc., Wayne, PA 19087. INTUNIV is a registered trademark of Shire LLC. ©2013 Shire US Inc. This product is covered by US patents including 6,287,599; 6,811,794. Version: 08 2013
®